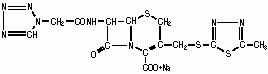 DRUG LABEL: Unknown
Manufacturer: ORCHID HEALTHCARE (A DIVISION OF ORCHID CHEMICALS AND PHARMACEUTICALS LTD.)
Category: prescription | Type: HUMAN PRESCRIPTION DRUG LABELING
Date: 20071025

Cefazolin for Injection USP
"PHARMACY BULK PACKAGE-
NOT FOR DIRECT INFUSION"

DESCRIPTION

Cefazolin for injection is a semi-synthetic cephalosporin for parenteral administration. It is the sodium salt of 3-{[(5-methyl-1,3,4-thiadiazol-2-yl)thio]-methyl}-8-oxo-7-[2-(1H-tetrazol-1-yl) acetamido]-5-thia-1-azabicyclo [4.2.0]oct-2-ene-2-carboxylic acid.

Structural Formula:

Each vial contains 48 mg (2 mEq) of sodium/1 gram of cefazolin sodium. Cefazolin for injection, USP is white to off-white crystalline powder.

Cefazolin for injection, USP is supplied in 10 grams Pharmacy Bulk Packages. Each Pharmacy Bulk Package contains, cefazolin sodium equivalent to 10 grams of cefazolin.

A Pharmacy Bulk Package is sterile dosage form for parenteral use that contains many single doses. The contents are restricted for use in a pharmacy admixture service and are intended for the preparation of admixtures for intravenous use. NOT FOR DIRECT INJECTION. FURTHER DILUTION IS REQUIRED BEFORE USE.

CLINICAL PHARMACOLOGY

Studies have shown that following intravenous administration of Cefazolin for injection to normal volunteers, mean serum concentrations peaked at approximately 185 mcg/mL and were approximately 4 mcg/mL at 8 hours for a 1 gram dose.

The serum half-life for Cefazolin for injection is approximately 1.8 hours following IV administration.

In a study (using normal volunteers) of constant intravenous infusion with dosages of 3.5 mg/kg for 1 hour (approximately 250 mg) and 1.5 mg/kg the next 2 hours (approximately 100 mg), Cefazolin for injection produced a steady serum level at the third hour of approximately 28 mcg/mL.

Studies in patients hospitalized with infections indicate that Cefazolin for injection produces mean peak serum levels approximately equivalent to those seen in normal volunteers.

Bile levels in patients without obstructive biliary disease can reach or exceed serum levels by up to 5 times; however, in patients with obstructive biliary disease, bile levels of Cefazolin for injection are considerably lower than serum levels (< 1 mcg/mL).

In synovial fluid, the level of Cefazolin for injection becomes comparable to that reached in serum at about 4 hours after drug administration.

Studies of cord blood show prompt transfer of Cefazolin for injection across the placenta. Cefazolin for injection is present in very low concentrations in the milk of nursing mothers.

Cefazolin for injection is excreted unchanged in the urine. In the first 6 hours approximately 60% of the drug is excreted in the urine and this increases to 70% to 80% within 24 hours.

In patients undergoing peritoneal dialysis (2 L/hr.), Cefazolin for injection produced mean serum levels of approximately 10 and 30 mcg/mL after 24 hours’ instillation of a dialyzing solution containing 50 mg/L and 150 mg/L, respectively. Mean peak levels were 29 mcg/mL (range 13 to 44 mcg/mL) with 50 mg/L (3 patients), and 72 mcg/mL (range 26 to 142 mcg/mL) with 150 mg/L (6 patients). Intraperitoneal administration of Cefazolin for injection is usually well tolerated.

Controlled studies on adult normal volunteers, receiving 1 gram 4 times a day for 10 days, monitoring CBC, SGOT, SGPT, bilirubin, alkaline phosphatase, BUN, creatinine and urinalysis, indicated no clinically significant changes attributed to Cefazolin for injection.

Microbiology

In vitro tests demonstrate that the bactericidal action of cephalosporins results from inhibition of cell wall synthesis. Cefazolin has been shown to be active against most strains of the following microorganisms both in vitro and in clinical infections as described in the INDICATIONS AND USAGE section:

Aerobic Gram-positive microorganisms

Staphylococcus aureus (including penicillinase-producing strains)

Staphylococcus epidermidis

Streptococcus pneumoniae

Streptococcus pyogenes and other strains of Streptococci

NOTE: Methicillin-resistant staphylococci are uniformly resistant to cefazolin. Many Enterococcus strains are resistant to cefazolin.

Aerobic Gram-negative microorganisms

Escherichia coli

Haemophilus influenzae

Klebsiella species

Proteus mirabilis

NOTE: Most strains of indole positive Proteus (Proteus vulgaris), Enterobacter cloacae, Morganella morganii and Providencia rettgeri are resistant. Serratia, Pseudomonas, Mima and Herellea species are almost uniformly resistant to cefazolin.

Susceptibility Testing

Dilution Techniques

Quantitative methods are used to determine antimicrobial minimum inhibitory concentrations (MICs). These MICs provide estimates of the susceptibility of bacteria to antimicrobial compounds. The MICs should be determined using a standardized procedure. Standardized procedures are based on a dilution method [National Committee for Clinical Laboratory Standards, Method for Dilution Antimicrobial Susceptibility Tests for Bacteria that Grow Aerobically – Fifth Edition. Approved Standard NCCLS Document M7-A4, Vol. 20, No.2, NCCLS, Wayne, PA, January 2000.] (broth) or equivalent with standardized inoculum concentrations and standardized concentrations of cefazolin powder. The MIC values should be interpreted according to the following criteria:

For Enterobacteriaceae and Staphylococcus spp.

MIC (mcg/mL) | Interpretation
< 8 | Susceptible (S)
16 | Intermediate (I)
> 32 | Resistant (R)

A report of “Susceptible” indicates that the pathogen is likely to be inhibited if the antimicrobial compound in the blood reaches the concentrations usually achievable. A report of “Intermediate” indicates that the result should be considered equivocal, and, if the microorganism is not fully susceptible to alternative, clinically feasible drugs, the test should be repeated. This category implies possible clinical applicability in body sites where the drug is physiologically concentrated or in situations where high dosage of drug can be used. This category also provides a buffer zone which prevents small uncontrolled technical factors from causing major discrepancies in interpretation. A report of “Resistant” indicates that the pathogen is not likely to be inhibited if the antimicrobial compound in the blood reaches the concentrations usually achievable; other therapy should be selected.

Standardized susceptibility test procedures require the use of laboratory control microorganisms to control the technical aspects of the laboratory procedures. Standard cefazolin powder should provide the following MIC values:

Microorganism |  | MIC (mcg/mL)
S. aureus | ATCC 29213 | 0.25 to 1
E. coli | ATCC 25922 | 1 to 4

Diffusion Techniques

Quantitative methods that require measurement of zone diameters also provide reproducible estimates of the susceptibility of bacteria to antimicrobial compounds. One such standardized procedure [National Committee for Clinical Laboratory Standards, Performance Standards for Antimicrobial Disk Susceptibility Tests – Seventh Edition. Approved Standard NCCLS Document M2-A7, Vol. 20, No. 1, NCCLS, Wayne, PA January 2000.] requires the use of standardized inoculum concentrations. This procedure uses paper disks impregnated with 30 mcg cefazolin to test the susceptibility of microorganisms to cefazolin.

Reports from the laboratory providing results of the standard single-disk susceptibility test with a 30 mcg cefazolin disk should be interpreted according to the following criteria:

For Enterobacteriaceae using the 30 mcg cefazolin disk

Zone diameter (mm) | Interpretation
> 18 | Susceptible (S)
15 to 17 | Intermediate (I)
< 14 | Resistant (R)

For Staphylococcus spp, using the 30 mcg cefazolin or the 30 mcg cephalothin disks

Zone diameter (mm) | Interpretation
> 18 | Susceptible (S)
15 to 17 | Intermediate (I)
< 14 | Resistant (R)

Interpretation should be as stated above for results using dilution techniques.

Interpretation involves correlation of the diameter obtained in the disk test with the MIC for cefazolin.

As with standardized dilution techniques, diffusion methods require the use of laboratory control microorganisms that are used to control the technical aspects of the laboratory procedures. For the diffusion technique, the 30 mcg cefazolin disk should provide the following zone diameter in this laboratory test quality control strain:

Microorganism |  | Zone diameter (mm)
S. aureus | ATCC 25923 | 29 to 35
E. coli | ATCC 25922 | 23 to 29

INDICATIONS AND USAGE

Cefazolin for injection is indicated in the treatment of the following serious infections due to susceptible organisms:

Respiratory Tract Infections due to S. pneumoniae, Klebsiella species, H. influenzae, S. aureus (penicillin-sensitive and penicillin-resistant), and group A beta-hemolytic streptococci.

Injectable benzathine penicillin is considered to be the drug of choice in treatment and prevention of streptococcal infections, including the prophylaxis of rheumatic fever.

Cefazolin for injection is effective in the eradication of streptococci from the nasopharynx; however, data establishing the efficacy of Cefazolin for injection in the subsequent prevention of rheumatic fever are not available at present.

Urinary Tract Infections due to E. coli, P. mirabilis, Klebsiella species, and some strains of enterobacter and enterococci.

Skin and Skin Structure Infections due to S. aureus (penicillin-sensitive and penicillin-resistant), group A beta-hemolytic streptococci, and other strains of streptococci.

Biliary Tract Infections due to E. coli, various strains of streptococci, P. mirabilis, Klebsiella species, and S. aureus.

Bone and Joint Infections due to S. aureus.

Genital Infections (i.e., prostatitis, epididymitis) due to E. coli, P. mirabilis, Klebsiella species, and some strains of enterococci.

Septicemia due to S. pneumoniae, S. aureus (penicillin-sensitive and penicillin-resistant), P. mirabilis, E. coli, and Klebsiella species.

Endocarditis due to S. aureus (penicillin-sensitive and penicillin-resistant) and group A beta-hemolytic streptococci.

Perioperative Prophylaxis the prophylactic administration of Cefazolin for injection preoperatively, intraoperatively, and postoperatively may reduce the incidence of certain postoperative infections in patients undergoing surgical procedures which are classified as contaminated or potentially contaminated (e.g., vaginal hysterectomy, and cholecystectomy in high-risk patients such as those older than 70 years, with acute cholecystitis, obstructive jaundice, or common duct bile stones).

The perioperative use of Cefazolin for injection may also be effective in surgical patients in whom infection at the operative site would present a serious risk (e.g., during open-heart surgery and prosthetic arthroplasty).

The prophylactic administration of Cefazolin for injection should usually be discontinued within a 24 hour period after the surgical procedure. In surgery where the occurrence of infection may be particularly devastating (e.g., open-heart surgery and prosthetic arthroplasty), the prophylactic administration of Cefazolin for injection may be continued for 3 to 5 days following the completion of surgery.

If there are signs of infection, specimens for cultures should be obtained for the identification of the causative organism so that appropriate therapy may be instituted.(See DOSAGE AND ADMINISTRATION.)

To reduce the development of drug-resistant bacteria and maintain the effectiveness of Cefazolin for injection and other antibacterial drugs, Cefazolin for injection should be used only to treat or prevent infections that are proven or strongly suspected to be caused by susceptible bacteria. When culture and susceptibility information are available, they should be considered in selecting or modifying antibacterial therapy. In the absence of such data, local epidemiology and susceptibility patterns may contribute to the empiric selection of therapy.

CONTRAINDICATIONS

CEFAZOLIN FOR INJECTION IS CONTRAINDICATED IN PATIENTS WITH KNOWN ALLERGY TO THE CEPHALOSPORIN GROUP OF ANTIBIOTICS.

WARNINGS

BEFORE THERAPY WITH CEFAZOLIN FOR INJECTION IS INSTITUTED, CAREFUL INQUIRY SHOULD BE MADE TO DETERMINE WHETHER THE PATIENT HAS HAD PREVIOUS HYPERSENSITIVITY REACTIONS TO CEFAZOLIN, CEPHALOSPORINS, PENICILLINS, OR OTHER DRUGS. IF THIS PRODUCT IS GIVEN TO PENICILLIN-SENSITIVE PATIENTS, CAUTION SHOULD BE EXERCISED BECAUSE CROSS-HYPERSENSITIVITY AMONG BETA-LACTAM ANTIBIOTICS HAS BEEN CLEARLY DOCUMENTED AND MAY OCCUR IN UP TO 10% OF PATIENTS WITH A HISTORY OF PENICILLIN ALLERGY. IF AN ALLERGIC REACTION TO CEFAZOLIN FOR INJECTION OCCURS, DISCONTINUE TREATMENT WITH THE DRUG. SERIOUS ACUTE HYPERSENSITIVITY REACTIONS MAY REQUIRE TREATMENT WITH EPINEPHRINE AND OTHER EMERGENCY MEASURES, INCLUDING OXYGEN, IV FLUIDS, IV ANTIHISTAMINES, CORTICOSTEROIDS, PRESSOR AMINES, AND AIRWAY MANAGEMENT, AS CLINICALLY INDICATED.

Pseudomembranous colitis has been reported with nearly all antibacterial agents, including cefazolin, and may range in severity from mild to life-threatening. Therefore, it is important to consider this diagnosis in patients who present with diarrhea subsequent to the administration of antibacterial agents.

Treatment with antibacterial agents alters the normal flora of the colon and may permit overgrowth of clostridia. Studies indicate that a toxin produced by Clostridium difficile is a primary cause of "antibiotic-associated colitis.”

After the diagnosis of pseudomembranous colitis has been established, therapeutic measures should be initiated. Mild cases of pseudomembranous colitis usually respond to drug discontinuation alone. In moderate to severe cases, consideration should be given to management with fluids and electrolytes, protein supplementation, and treatment with an oral antibacterial drug clinically effective against C.difficile colitis.

PRECAUTIONS

General

Prolonged use of Cefazolin for injection may result in the overgrowth of nonsusceptible organisms. Careful clinical observation of the patient is essential.

When Cefazolin for injection is administered to patients with low urinary output because of impaired renal function, lower daily dosage is required (see DOSAGE AND ADMINISTRATION).

As with other β-lactam antibiotics, seizures may occur if inappropriately high doses are administered to patients with impaired renal function (see DOSAGE AND ADMINISTRATION).

Cefazolin for injection, as with all cephalosporins, should be prescribed with caution in individuals with a history of gastrointestinal disease, particularly colitis.

Cephalosporins may be associated with a fall in prothrombin activity. Those at risk include patients with renal or hepatic impairment or poor nutritional state, as well as patients receiving a protracted course of antimicrobial therapy, and patients previously stabilized on anticoagulant therapy. Prothrombin time should be monitored in patients at risk and exogenous vitamin K administered as indicated.

Prescribing Cefazolin for injection in the absence of a proven or strongly suspected bacterial infection or a prophylactic indication is unlikely to provide benefit to the patient and increase the risk of the development of drug-resistant bacteria.

Drug Interactions

Probenecid may decrease renal tubular secretion of cephalosporins when used concurrently, resulting in increased and more prolonged cephalosporin blood levels.

Drug/Laboratory Test Interactions

A false positive reaction for glucose in the urine may occur with Benedict's solution, Fehling’s solution or with CLINITEST® tablets, but not with enzyme-based tests such as CLINISTIX®.

Positive direct and indirect antiglobulin (Coombs) tests have occurred; these may also occur in neonates whose mothers received cephalosporins before delivery.

Information for Patients

Patients should be counseled that antibacterial drugs including Cefazolin for injection, should only be used to treat bacterial infections. They do not treat viral infections (e.g., the common cold). When Cefazolin for injection is prescribed to treat a bacterial infection, patients should be told that although it is common to feel better early in the course of therapy, the medication should be taken exactly as directed. Skipping doses or not completing the full course of therapy may: (1) decrease the effectiveness of the immediate treatment, and (2) increase the likelihood that bacteria will develop resistance and will not be treatable by Cefazolin for injection or other antibacterial drugs in the future.

Carcinogenesis/Mutagenesis

Mutagenicity studies and long-term studies in animals to determine the carcinogenic potential of Cefazolin for injection have not been performed.

Pregnancy

Teratogenic Effects

Pregnancy Category B

Reproduction studies have been performed in rats, mice and rabbits at doses up to 25 times the human dose and have revealed no evidence of impaired fertility or harm to the fetus due to Cefazolin for injection. There are, however, no adequate and well-controlled studies in pregnant women. Because animal reproduction studies are not always predictive of human response, this drug should be used during pregnancy only if clearly needed.

Labor and Delivery

When cefazolin has been administered prior to caesarean section, drug levels in cord blood have been approximately one quarter to one third of maternal drug levels. The drug appears to have no adverse effect on the fetus.

Nursing Mothers

Cefazolin for injection is present in very low concentrations in the milk of nursing mothers. Caution should be exercised when Cefazolin for injection is administered to a nursing woman.

Pediatric Use

Safety and effectiveness for use in premature infants and neonates have not been established. See DOSAGE AND ADMINISTRATION for recommended dosage in pediatric patients older than 1 month.

Geriatric Use

Of the 920 subjects who received Cefazolin for injection in clinical studies, 313 (34%) were 65 years and over, while 138 (15%) were 75 years and over. No overall differences in safety or effectiveness were observed between these subjects and younger subjects. Other reported clinical experience has not identified differences in responses between the elderly and younger patients, but greater sensitivity of some older individuals cannot be ruled out.

This drug is known to be substantially excreted by the kidney, and the risk of toxic reactions to this drug may be greater in patients with impaired renal function. Because elderly patients are more likely to have decreased renal function, care should be taken in dose selection, and it may be useful to monitor renal function (see PRECAUTIONS, General and DOSAGE and ADMINISTRATION).

ADVERSE REACTIONS

The following reactions have been reported:

Gastrointestinal

Diarrhea, oral candidiasis (oral thrush), vomiting, nausea, stomach cramps, anorexia, and pseudomembranous colitis. Onset of pseudomembranous colitis symptoms may occur during or after antibiotic treatment (see WARNINGS). Nausea and vomiting have been reported rarely.

Allergic

Anaphylaxis, eosinophilia, itching, drug fever, skin rash, Stevens-Johnson syndrome.

Hematologic

Neutropenia, leukopenia, thrombocytopenia, thrombocythemia.

Hepatic

Transient rise in SGOT, SGPT and alkaline phosphatase levels has been observed. As with other cephalosporins, reports of hepatitis have been received.

Renal

As with other cephalosporins, reports of increased BUN and creatinine levels, as well as renal failure, have been received.

Local Reactions

Rare instances of phlebitis have been reported at site of injection. Some induration has occurred.

Other Reactions

Genital and anal pruritus (including vulvar pruritus, genital moniliasis, and vaginitis).

Cephalosporin-class Adverse Reactions

In addition to the adverse reactions listed above that have been observed in patients treated with cefazolin, the following adverse reactions and altered laboratory tests have been reported for cephalosporin-class antibiotics:

Adverse Reactions: Allergic reactions, urticaria, serum sickness-like reaction, erythema multiforme, toxic epidermal necrolysis, colitis, renal dysfunction, toxic nephropathy, abdominal pain, reversible hyperactivity, hypertonia, hepatic dysfunction including cholestasis, aplastic anemia, hemolytic anemia, hemorrhage, and superinfection.

Altered Laboratory Tests: Prolonged prothrombin time, positive direct Coombs’ test, false-positive test for urinary glucose, elevated bilirubin, elevated LDH, increased creatinine, pancytopenia, and agranulocytosis.

Several cephalosporins have been implicated in triggering seizures, particularly in patients with renal impairment when the dosage was not reduced (see DOSAGE AND ADMINISTRATION). If seizures associated with drug therapy occur, the drug should be discontinued. Anticonvulsant therapy can be given if clinically indicated.

DOSAGE AND ADMINISTRATION

Usual Adult Dosage

Type of Infection | Dose | Frequency
Moderate to severe infections | 500mg to 1gram | every 6 to 8 hrs.
Mild infections caused by susceptible gram-positive cocci | 250 mg to 500 mg | every 8 hours
Acute, uncomplicated urinary tract infections | 1 gram | every 12 hours
Pneumococcal pneumonia | 500 mg | every 12 hours
Severe, life-threatening infections (e.g., endocarditis, septicemia) [ln rare instances, doses of up to 12 grams of Cefazolin for injection per day have been used.] | 1 gram to 1.5 grams | every 6 hours

Perioperative Prophylactic Use

To prevent postoperative infection in contaminated or potentially contaminated surgery, recommended doses are:

1. 1 gram IV administered ^1/2 hour to 1 hour prior to the start of surgery.
2. For lengthy operative procedures (e.g., 2 hours or more), 500 mg to 1 gram IV during surgery (administration modified depending on the duration of the operative procedure).
3. 500 mg to 1 gram IV every 6 to 8 hours for 24 hours postoperatively.

It is important that (1) the preoperative dose be given just (^1/2 to 1 hour) prior to the start of surgery so that adequate antibiotic levels are present in the serum and tissues at the time of initial surgical incision; and (2) Cefazolin for injection be administered, if necessary, at appropriate intervals during surgery to provide sufficient levels of the antibiotic at the anticipated moments of greatest exposure to infective organisms.

In surgery where the occurrence of infection may be particularly devastating (e.g., open-heart surgery and prosthetic arthroplasty), the prophylactic administration of Cefazolin for injection may be continued for 3 to 5 days following the completion of surgery.

Dosage Adjustment for Patients with Reduced Renal Function

Cefazolin for injection may be used in patients with reduced renal function with the following dosage adjustments: Patients with a creatinine clearance of 55 mL/min. or greater or a serum creatinine of 1.5 mg % or less can be given full doses. Patients with creatinine clearance rates of 35 to 54 mL/min. or serum creatinine of 1.6 to 3 mg % can also be given full doses but dosage should be restricted to at least 8 hour intervals. Patients with creatinine clearance rates of 11 to 34 mL/min. or serum creatinine of 3.1 to 4.5 mg % should be given ^1/2 the usual dose every 12 hours. Patients with creatinine clearance rates of 10 mL/min. or less or serum creatinine of 4.6 mg % or greater should be given ^1/2 the usual dose every 18 to 24 hours. All reduced dosage recommendations apply after an initial loading dose appropriate to the severity of the infection. Patients undergoing peritoneal dialysis: See CLINICAL PHARMACOLOGY.

Pediatric Dosage

In pediatric patients, a total daily dosage of 25 to 50 mg per kg (approximately 10 to 20 mg per pound) of body weight, divided into 3 or 4 equal doses, is effective for most mild to moderately severe infections. Total daily dosage may be increased to 100 mg per kg (45 mg per pound) of body weight for severe infections. Since safety for use in premature infants and in neonates has not been established, the use of Cefazolin for injection in these patients is not recommended.

Pediatric Dosage Guide
Weight |  | 25 mg/kg/day Divided into 3 Doses |  | 25 mg/kg/day Divided into 4 Doses
Lbs | Kg | Approximate Single Dose mg/q8h | Vol.(mL) needed with dilution of 125 mg/mL | Approximate Single Dose mg/q6h | Vol.(mL) needed with dilution of 125 mg/mL
10 | 4.5 | 40 mg | 0.35 mL | 30 mg | 0.25 mL
20 | 9 | 75 mg | 0.6 mL | 55 mg | 0.45 mL
30 | 13.6 | 115 mg | 0.9 mL | 85 mg | 0.7 mL
40 | 18.1 | 150 mg | 1.2 mL | 115 mg | 0.9 mL
50 | 22.7 | 190 mg | 1.5 mL | 140 mg | 1.1 mL

Weight |  | 50 mg/kg/day Divided into 3 Doses |  | 50 mg/kg/day Divided into 4 Doses
Lbs | Kg | Approximate Single Dose mg/q8h | Vol.(mL) needed with dilution of 225 mg/mL | Approximate Single Dose mg/q6h | Vol.(mL) needed with dilution of 225 mg/mL
10 | 4.5 | 75 mg | 0.35 mL | 55 mg | 0.25 mL
20 | 9 | 150 mg | 0.7 mL | 110 mg | 0.5 mL
30 | 13.6 | 225 mg | 1 mL | 170 mg | 0.75 mL
40 | 18.1 | 300 mg | 1.35 mL | 225 mg | 1 mL
50 | 22.7 | 375 mg | 1.7 mL | 285 mg | 1.25 mL

In pediatric patients with mild to moderate renal impairment (creatinine clearance of 70 to 40 mL/min.), 60 percent of the normal daily dose given in equally divided doses every 12 hours should be sufficient. In patients with moderate impairment (creatinine clearance of 40 to 20 mL/min.), 25 percent of the normal daily dose given in equally divided doses every 12 hours should be adequate. Pediatric patients with severe renal impairment (creatinine clearance of 20 to 5 mL/min.) may be given 10 percent of the normal daily dose every 24 hours. All dosage recommendations apply after an initial loading dose.

RECONSTITUTION

Preparation of Parenteral Solution

Parenteral drug products should be SHAKEN WELL when reconstituted, and inspected visually for particulate matter prior to administration. If particulate matter is evident in reconstituted fluids, the drug solutions should be discarded.

Reconstituted solutions may range in color from pale yellow to yellow without a change in potency.

Directions for Proper Use of a Pharmacy Bulk Package

Not for direct infusion. This Pharmacy Bulk Package is for use in a hospital pharmacy admixture service, only in a suitable work area, such as a laminar flow hood. Using aseptic technique, the container may be penetrated only one time using a suitable sterile dispensing set or transfer device that allows measured dispensing of the contents. Use of a syringe and needle is not recommended as it may cause leakage. The withdrawal of container contents should be accomplished without delay. However, should this not be possible, a maximum time of 4 HOURS from initial closure entry is permitted to complete fluid transfer operations. This time limit should begin with the introduction of the solvent or diluent into the Pharmacy Bulk Package. DISCARD ANY UNUSED PORTION AFTER 4 HOURS.

THIS PHARMACY BULK PACKAGE IS NOT INTENDED TO BE DISPENSED AS A UNIT

Pharmacy Bulk Package

Add Sterile Water for Injection, Bacteriostatic Water for Injection, or Sodium Chloride Injection according to the table below. SHAKE WELL. Use promptly. (Discard vial within 4 hours after initial entry.)

Vial Size | Amount of Diluent | Approximate Concentration | Approximate Available Volume
10 grams | 45 mL | 1 gram/5 mL | 51 mL
 | 96 mL | 1 gram/10 mL | 102 mL

ADMINISTRATION

Intravenous Administration

Intermittent or continuous infusion: Dilute reconstituted Cefazolin for injection in 50 to 100 mL of 1 of the following solutions:

Sodium Chloride Injection, USP

5% or 10% Dextrose Injection, USP

5% Dextrose in Lactated Ringer's Injection, USP

5% Dextrose and 0.9% Sodium Chloride Injection, USP

5% Dextrose and 0.45% Sodium Chloride Injection, USP

5% Dextrose and 0.2% Sodium Chloride Injection, USP

Lactated Ringer's Injection, USP

Invert Sugar 5% or 10% in Sterile Water for Injection

Ringer's Injection, USP

5% Sodium Bicarbonate Injection, USP

When reconstituted or diluted according to the instructions above, Cefazolin for injection is stable for 24 hours at room temperature or for 10 days if stored under refrigeration (5°C or 41 °F).

Prior to administration parenteral drug products should be inspected visually for particulate matter and discoloration whenever solution and container permit.

HOW SUPPLIED

Cefazolin for injection, USP

Each Pharmacy Bulk Package contains cefazolin sodium equivalent to 10 grams of cefazolin.

Cefazolin for injection is available as follows:

10 vials 10 grams/100 mL vials per carton (NDC 63304-941-10).

As with other cephalosporins, Cefazolin for injection tends to darken depending on storage conditions; within the stated recommendations, however, product potency is not adversely affected.

Store dry powder at 20° to 25° C (68° to 77°F) [See USP Controlled Room Temperature]. Before reconstitution PROTECT FROM LIGHT.

REFERENCES

1. National Committee for Clinical Laboratory Standards, Method for Dilution Antimicrobial Susceptibility Tests for Bacteria that Grow Aerobically – Fifth Edition. Approved Standard NCCLS Document M7-A4, Vol. 20, No.2, NCCLS, Wayne, PA, January 2000.
2. National Committee for Clinical Laboratory Standards, Performance Standards for Antimicrobial Disk Susceptibility Tests – Seventh Edition. Approved Standard NCCLS Document M2-A7, Vol. 20, No. 1, NCCLS, Wayne, PA January 2000.

CLINITEST is registered trademark of Miles, Inc.

CLINISTIX is a registered trademark of Bayer Corporation.

Manufactured for:

Ranbaxy Pharmaceuticals Inc.

Jacksonville, FL 32257 USA

by: Orchid Healthcare

(A Division of Orchid Chemicals & Pharmaceuticals Ltd.)

Irungattukottai, India 602 105

DATE OF ISSUANCE: SEPTEMBER 2006

948025510